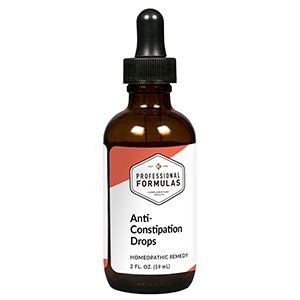 DRUG LABEL: Anti-Constipation Drops
NDC: 63083-2077 | Form: LIQUID
Manufacturer: Professional Complementary Health Formulas
Category: homeopathic | Type: HUMAN OTC DRUG LABEL
Date: 20190815

ACTIVE INGREDIENTS: MILK THISTLE 2 [hp_X]/59 mL; CHELIDONIUM MAJUS WHOLE 2 [hp_X]/59 mL; CINCHONA OFFICINALIS BARK 3 [hp_X]/59 mL; BRYONIA ALBA ROOT 4 [hp_X]/59 mL; DIOSCOREA VILLOSA TUBER 4 [hp_X]/59 mL; LYCOPODIUM CLAVATUM SPORE 4 [hp_X]/59 mL; STRYCHNOS NUX-VOMICA SEED 4 [hp_X]/59 mL; CHOLESTEROL 6 [hp_X]/59 mL; CITRULLUS COLOCYNTHIS FRUIT PULP 6 [hp_X]/59 mL; SODIUM CHLORIDE 6 [hp_X]/59 mL; GRAPHITE 12 [hp_X]/59 mL; LEAD 12 [hp_X]/59 mL
INACTIVE INGREDIENTS: ALCOHOL; WATER

C77

ACTIVE INGREDIENTS

Carduus marianus 2X
Chelidonium majus 2X
Cinchona officinalis 3X
Bryonia 4X
Dioscorea villosa 4X
Lycopodium clavatum 4X
Nux vomica 4X
Cholesterinum 6X
Colocynthis 6X
Natrum muriaticum 6X, 60X
Graphites 12X
Plumbum metallicum 12X

QUESTIONS

Professional Formulas

PO Box 2034 Lake Oswego, OR 97035

INDICATIONS

For the temporary relief of occasional constipation, bloating, flatulence, bitter taste, or lack of appetite.*

PURPOSE

*Claims based on traditional homeopathic practice, not accepted medical evidence. Not FDA evaluated.

WARNINGS

Consult a doctor if condition worsens or if symptoms persist. Keep out of the reach of children. In case of overdose, get medical help or contact a poison control center right away. If pregnant or breastfeeding, ask a healthcare professional before use.

Keep out of the reach of children.

PREGNANCY OR BREAST FEEDING

If pregnant or breastfeeding, ask a healthcare professional before use.

DIRECTIONS

Place drops under tongue 30 minutes before/after meals. Adults and children 12 years and over: Take 10 drops up to 3 times per day for up to 6 weeks. For immediate onset of symptoms, take 10 to 15 drops every 15 minutes up to 3 hours. For less severe symptoms, take 10-15 drops hourly up to 8 hours. Consult a physician for use in children under 12 years of age.

OTHER INFORMATION

Tamper resistant. If seal is broken, do not use. After opening, close container tightly and store at room temperature away from heat.

INACTIVE INGREDIENTS

20% ethanol, purified water.

LABEL

Est 1985

Professional Formulas

Complementary Health

Anti-Constipation Drops

Homeopathic Remedy

2 FL. OZ. (59 mL)